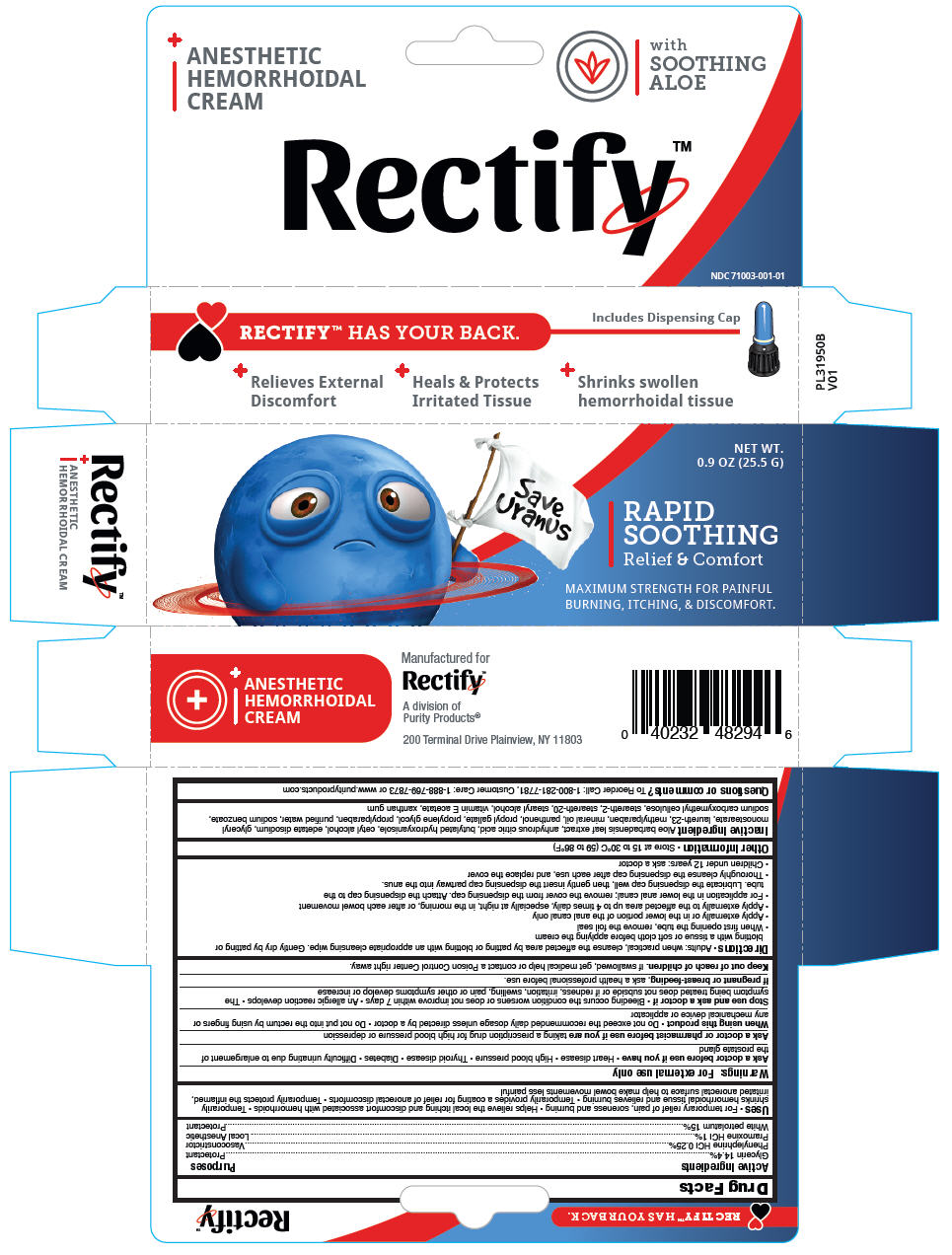 DRUG LABEL: Hemorrhoidal
NDC: 71003-001 | Form: CREAM
Manufacturer: Purity Products
Category: otc | Type: HUMAN OTC DRUG LABEL
Date: 20161025

ACTIVE INGREDIENTS: GLYCERIN 144 mg/1 g; PHENYLEPHRINE HYDROCHLORIDE 2.5 mg/1 g; PRAMOXINE HYDROCHLORIDE 10 mg/1 g; PETROLATUM 150 mg/1 g
INACTIVE INGREDIENTS: ALOE VERA LEAF; BUTYLATED HYDROXYANISOLE; CETYL ALCOHOL; CITRIC ACID MONOHYDRATE; EDETATE DISODIUM ANHYDROUS; GLYCERYL MONOSTEARATE; LAURETH-23; METHYLPARABEN; MINERAL OIL; PANTHENOL; PROPYL GALLATE; PROPYLENE GLYCOL; PROPYLPARABEN; SODIUM BENZOATE; CARBOXYMETHYLCELLULOSE SODIUM, UNSPECIFIED FORM; STEARETH-2; STEARETH-20; STEARYL ALCOHOL; .ALPHA.-TOCOPHEROL; WATER; XANTHAN GUM

Hemorrhoidal Cream
Anesthetic

Drug Facts

ACTIVE INGREDIENT

PURPOSE

Active Ingredients | Purposes
Glycerin 14.4% | Protectant
Phenylephrine HCl 0.25% | Vasoconstrictor
Pramoxine HCl 1% | Local Anesthetic
White petrolatum 15% | Protectant

Uses

- For temporary relief of pain, soreness and burning
- Helps relieve the local itching and discomfort associated with hemorrhoids
- Temporarily shrinks hemorrhoidal tissue and relieves burning
- Temporarily provides a coating for relief of anorectal discomforts
- Temporarily protects the inflamed, irritated anorectal surface to help make bowel movements less painful

Warnings

For external use only

Ask a doctor before use if you have

- Heart disease
- High blood pressure
- Thyroid disease
- Diabetes
- Difficulty urinating due to enlargement of the prostate gland

Ask a doctor or pharmacist before use if you are taking a prescription drug for high blood pressure or depression

When using this product

- Do not exceed the recommended daily dosage unless directed by a doctor
- Do not put into the rectum by using fingers or any mechanical device or applicator

Stop use and ask a doctor if

- Bleeding occurs the condition worsens or does not improve within 7 days
- An allergic reaction develops
- The symptom being treated does not subside or if redness, irritation, swelling, pain or other symptoms develop or increase

PREGNANCY OR BREAST FEEDING

If pregnant or breast-feeding, ask a health professional before use.

Keep out of reach of children. If swallowed, get medical help or contact a Poison Control Center right away.

Directions

- Adults: when practical, cleanse the affected area by patting or blotting with an appropriate cleansing wipe. Gently dry by patting or blotting with a tissue or soft cloth before applying the cream
- When first opening the tube, remove the foil seal
- Apply externally or in the lower portion of the anal canal only
- Apply externally to the affected area up to 4 times daily, especially at night, in the morning, or after each bowel movement
- For application in the lower anal canal; remove the cover from the dispensing cap. Attach the dispensing cap to the tube. Lubricate the dispensing cap well, then gently insert the dispensing cap partway into the anus.
- Thoroughly cleanse the dispensing cap after each use, and replace the cover
- Children under 12 years: ask a doctor

Other Information

- Store at 15 to 30°C (59 to 86°F)

Inactive Ingredient

Aloe barbadensis leaf extract, anhydrous citric acid, butylated hydroxyanisole, cetyl alcohol, edetate disodium, glyceryl monostearate, laureth-23, methylparaben, mineral oil, panthenol, propyl gallate, propylene glycol, propylparaben, purified water, sodium benzoate, sodium carboxymethyl cellulose, steareth-2, steareth-20, stearyl alcohol, vitamin E acetate, xanthan gum

Questions or comments?

To Reorder Call: 1-800-281-7781, Customer Care: 1-888-769-7873 or www.purityproducts.com

PRINCIPAL DISPLAY PANEL - 25.5 G Tube Carton

NET WT.
0.9 OZ (25.5 G)

Save
Uranus

RAPID
SOOTHING
Relief & Comfort

MAXIMUM STRENGTH FOR PAINFUL
BURNING, ITCHING, & DISCOMFORT.